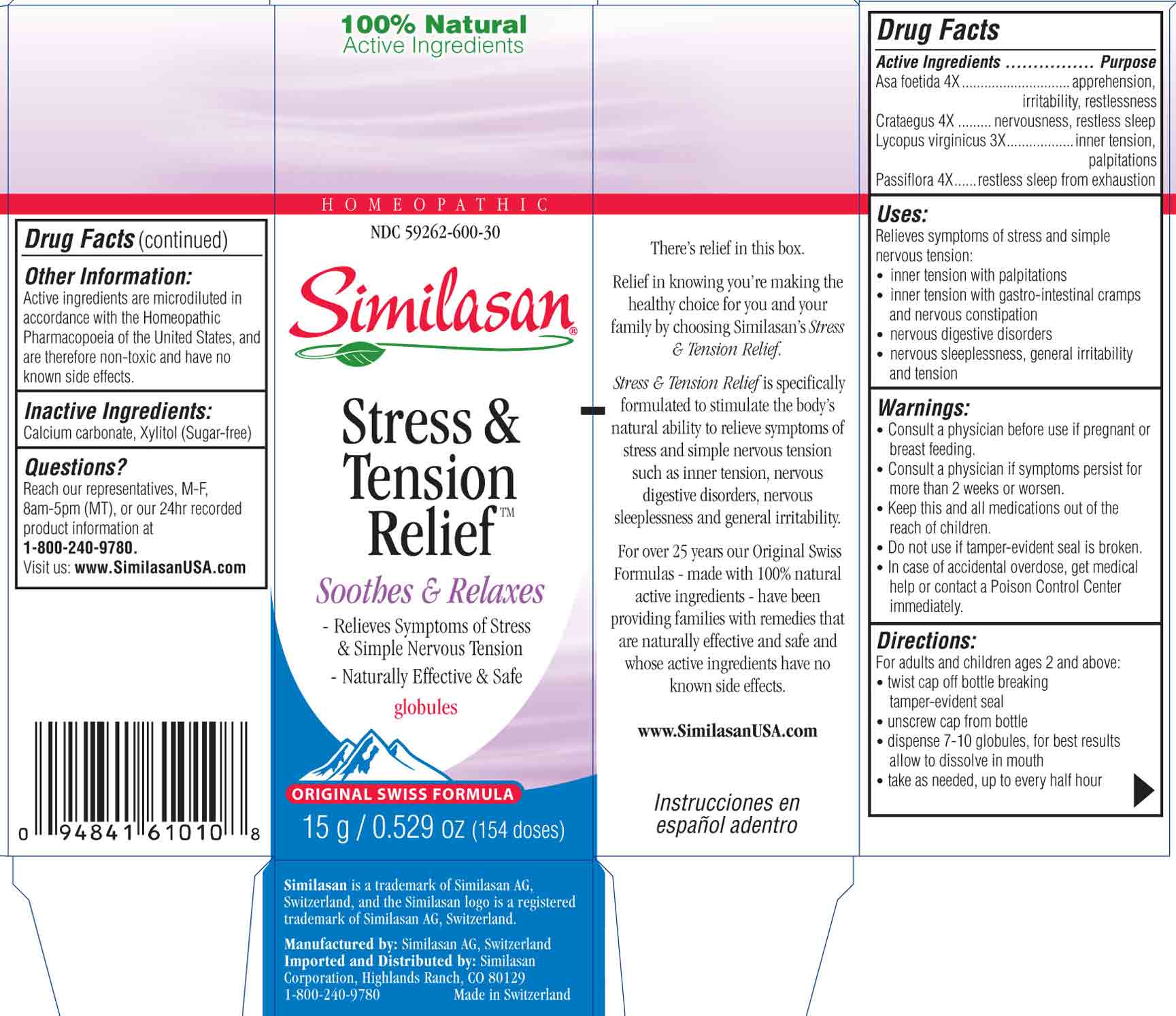 DRUG LABEL: Stress and Tension Relief
NDC: 59262-600 | Form: GLOBULE
Manufacturer: Similasan Corporation
Category: homeopathic | Type: HUMAN OTC DRUG LABEL
Date: 20130731

ACTIVE INGREDIENTS: ASAFETIDA 4 [hp_X]/1 1; CRATAEGUS FRUIT 4 [hp_X]/1 1; LYCOPUS VIRGINICUS 3 [hp_X]/1 1; PASSIFLORA INCARNATA FLOWERING TOP 4 [hp_X]/1 1
INACTIVE INGREDIENTS: CALCIUM CARBONATE; XYLITOL

Stress and Tension Relief

Active ingredient(s)

Asa foetida 4X

Purpose

apprehension, irritability, restlessness

Active ingredient(s)

Crataegus 4X

Purpose

nervousness, restless sleep

Active ingredient(s)

Lycopus virginicus 3X

Purpose

inner tension, palpitations

Active ingredient(s)

Passiflora 4X

Purpose

restless sleep from exhaustion

Uses:

Relieves symptoms of stress and simple nervous tension-
- inner tension with palpitations
- inner tension with gastro-intestinal cramps and nervous constipation
- nervous digestive disorders
- nervous sleeplessness, general irritability and tension

Warnings:

- Consult a physician before use if pregnant or breast feeding.
- Consult a physician if symptoms persist for more than 2 weeks or worsen.
- Keep this and all medications out of the reach of children.
- Do not use if tamper-evident seal is broken.
- In case of accidental overdose, get medical help or contact a Poison Control Center immediately.

Keep out of reach of children

Keep this and all medications out of the reach of children

Directions:

For adults and children ages 2 and above:
- twist cap off bottle breaking tamper-evident seal
- unscrew cap from bottle
- dispense 7-10 globules, for best results allow to dissolve in moith
- take as needed up to every half hour

Other information:

Active ingredients are microdiluted in accordance with the Homeopathic Pharmacopoeia of the United States, and are therefore non-toxic and have no known side effects.

Inactive ingredients:

Calcium carbonate, Xylitol (Sugar-free)

Questions?

Call 1-800-240-9780 for 24hr recorded product information. Representatives available, M-F, 8am-5pm (MT), or visit: www.SimilasanUSA.com

Principal Display Panel

NDC 59262-600-30
Similasan
Stress & Tension Relief
Globules
15g/ 0.529 oz

Stress and Tension Relief box